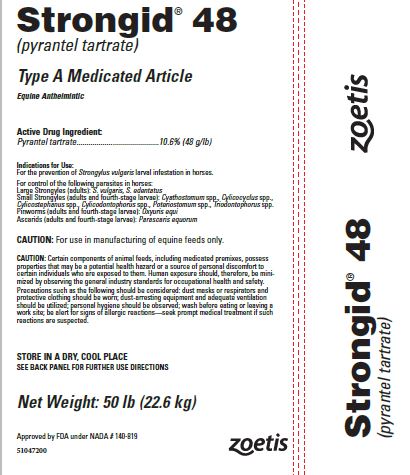 DRUG LABEL: Strongid
NDC: 54771-0459 | Form: GRANULE
Manufacturer: Zoetis Inc.
Category: animal | Type: OTC TYPE A MEDICATED ARTICLE ANIMAL DRUG LABEL
Date: 20230823

ACTIVE INGREDIENTS: PYRANTEL TARTRATE 105.8 g/1 kg

Strongid® 48

Strongid® 48
(pyrantel tartrate)

Type A Medicated Article

Equine Anthelmintic

Active Drug Ingredient:

Pyrantel tartrate.........................................10.6% (48 g/lb)

Indications for Use:

For the prevention of Strongylus vulgaris larval infestation in horses.

For control of the following parasites in horses:
Large Strongyles (adults): S. vulgaris, S. edentatus
Small Strongyles (adults and fourth-stage larvae): Cyathostomum spp., Cylicocyclus spp., Cylicostephanus spp., Cylicodontophorus spp., Poteriostomum spp., Triodontophorus spp.
Pinworms (adults and fourth-stage larvae): Oxyuris equi
Ascarids (adults and fourth-stage larvae): Parascaris equorum

CAUTION:

CAUTION: For use in manufacturing of equine feeds only.

CAUTION: Certain components of animal feeds, including medicated premixes, possess properties that may be a potential health hazard or a source of personal discomfort to certain individuals who are exposed to them. Human exposure should, therefore, be minimized by observing the general industry standards for occupational health and safety.
Precautions such as the following should be considered: dust masks or respirators and protective clothing should be worn; dust-arresting equipment and adequate ventilation should be utilized; personal hygiene should be observed; wash before eating or leaving a work site; be alert for signs of allergic reactions—seek prompt medical treatment if such reactions are suspected.

Storage

STORE IN A DRY, COOL PLACE
SEE BACK PANEL FOR FURTHER USE DIRECTIONS

Net Weight: 50 lb (22.6 kg)

Approved by FDA under NADA # 140-819

51047200

Mixing and Use Directions

Strongid is to be administered on a continuous basis either as a top-dress or mixed in the horse’s daily grain ration at the rate of 1.2 mg/lb (2.64 mg/kg) of body weight daily. The duration of administration is for the period during which the horse is at risk of exposure to internal parasites.
Foals may be treated at such time when consistent intake of grain mix is occurring. This is generally between 2 and 3 months of age.
Strongid may be used in mares at any stage of pregnancy or lactation. Stallion fertility is not affected by the use of Strongid.
Do not underdose. Ensure each animal receives a complete dose based on a current body weight. Underdosing may result in ineffective treatment, and encourage the development of parasite resistance.

Typical Mixing Directions to Deliver 1.2 mg/lb (2.64 mg/kg)

lb of Medicated Grain Mix per 100 lb of Body Weight | lb of Strongid 48 | lb of Nonmedicated Feed | Resulting Concentration (g/ton)
2.00 | 2.5 | 1997.5 | 120
1.5 | 3.3 | 1996.7 | 160
0.50 | 10.0 | 1990.0 | 480
0.20 | 25.0 | 1975.0 | 1200

lb of Medicated Top-Dress per 100 lb of Body Weight | lb of Strongid 48 | lb of Nonmedicated Feed | Resulting Concentration (g/ton)
0.04 | 125.0 | 1875.0 | 6000
0.025 | 200.0 | 1800.0 | 9600
0.02 | 250.0 | 1750.0 | 12000
0.0125 | 400.0 | 1600.0 | 19200

WARNING

Do not use in horses intended for human consumption.

OTHER WARNINGS

Parasite resistance may develop to any dewormer, and has been reported for most classes of dewormers. Treatment with a dewormer used in conjunction with parasite management practices appropriate to the geographic area and the animal(s) to be treated may slow the development of parasite resistance. Fecal examinations or other diagnostic tests and parasite management history should be used to determine if the product is appropriate for the herd prior to the use of any dewormer. Following the use of any dewormer, effectiveness of treatment should be monitored (for example, with the use of a fecal egg count reduction test or another appropriate method). A decrease in a drug's effectiveness over time as calculated by fecal egg count reduction tests may indicate the development of resistance to the dewormer administered. Your parasite management plan should be adjusted accordingly based on regular monitoring.

CAUTION

Consult your veterinarian before using in severely debilitated animals and for assistance in the diagnosis, treatment, and control of parasitism. Do not mix in feeds containing bentonite.

51047200

Zoetis
Distributed by:
Zoetis Inc.
Kalamazoo, MI 49007
Product of Mexico